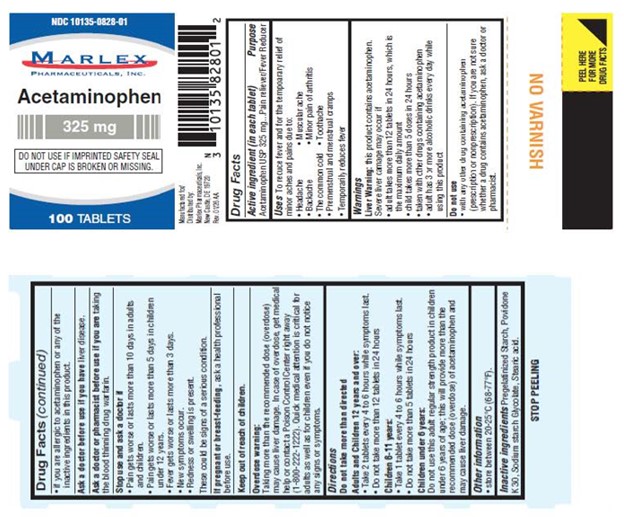 DRUG LABEL: Acetaminophen 325mg
NDC: 10135-828 | Form: TABLET
Manufacturer: Marlex Pharmaceuticals Inc
Category: otc | Type: HUMAN OTC DRUG LABEL
Date: 20260201

ACTIVE INGREDIENTS: ACETAMINOPHEN 325 mg/1 1
INACTIVE INGREDIENTS: POVIDONE K30; STARCH, CORN; STEARIC ACID; SODIUM STARCH GLYCOLATE TYPE A POTATO

Acetaminophen 325mg

Drug Facts

Active Ingredient (in each tablet)

Acetaminophen USP 325 mg

Purpose

Pain Reliever/Fever Reducer

Uses

To reduce fever and for the temporary relief of minor aches and pains due to:

- Headache
- Backache
- The common cold
- Premenstrual and menstrual cramps
- Temporarily reduces fever
- Muscular ache
- Minor pain of arthritis
- Toothache

Warnings

Liver warning:this product contains acetaminophen.

Severe liver damage may occur if

- adult takes more than 12 tablets in 24 hours, which is the maximum daily amount
- child takes more than 5 doeses in 24 hours
- taken with other drugs containing acetaminophen
- adult has 3 or more alcoholic drinks every day while using this product

Do not use

- with any other drug containing acetaminophen (prescription or nonprescription). If you are not sure whether a drug contains acetaminophen, ask a doctor or pharmacist.
- if you are allergic to acetaminophen or any of the inactive ingredients in this product.

Ask a Doctor

before use if you have liver disease.

Ask a doctor or pharmacist before use

if you are taking the blood thinning drug warfarin.

Stop use and ask a doctor if

- Pain gets worse or lasts more than 10 days in adults and children.
- Pain gets worse or lasts more than 5 days in children under 12 years.
- Fever gets worse or lasts more than 3 days.
- New symptoms occur.
- Redness or swelling is present.

These could be signs of a serious condition.

If pregnant or breast-feeding,

ask a health professional before use.

Overdose warning:

Taking more than the recommended dose (overdose) may cause liver damage. In case of overdose, get medical help or contact a Poison Control Center right away. (1-800-222-1222). Quick medical attention is critical for adults as well as for children even if you do not notice any signs or symptoms.

Directions

Do not take more than directed

Adults and Children 12 years and over:

- Take 2 tablets every 4 to 6 hours while symptoms last.
- Do not take more than 12 tablets in 24 hours

Children 6-11 years:

- Take 1 tablet every 4 to 6 hours while symptoms last.
- Do not take more than 5 tablets in 24 hours.

Children under 6 years:

Do not use this adult regular strength product in children under 6 years of age; this will provide more than the recommended dose (overdose) of acetaminophen and may cause liver damage.

Other Information

- Store between 20-25 ˚C (68-77 ˚F).

Inactive Ingredients

Pregelatinized Starch, Povidone K 30, Sodium starch Glycolate, Stearic Acid.

Manufactured for/ Distributed by:
Marlex Pharmaceuticals, Inc.
New Castle, DE 19720

Rev. 01/26 AA

PRINCIPAL DISPLAY PANEL

NDC 10135-0828-01
Acetaminophen
325 mg
100 TABLETS